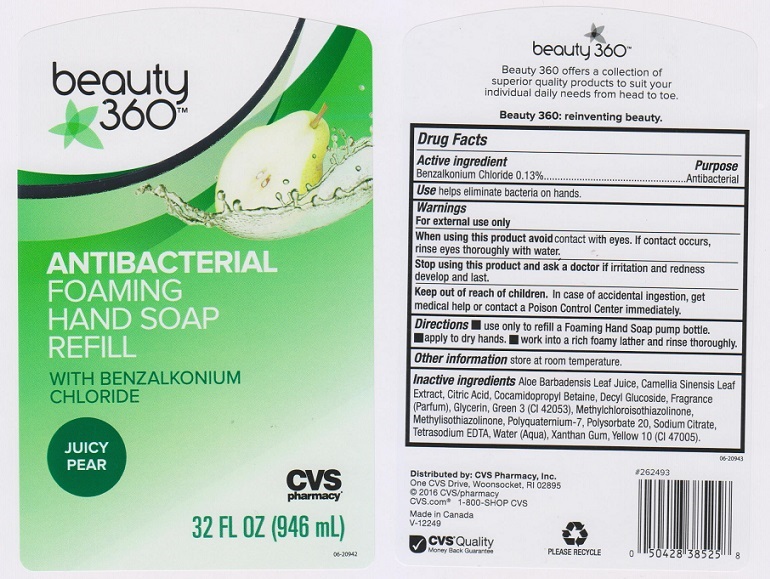 DRUG LABEL: CVS PHARMACY
NDC: 59779-113 | Form: LIQUID
Manufacturer: CVS PHARMACY
Category: otc | Type: HUMAN OTC DRUG LABEL
Date: 20160208

ACTIVE INGREDIENTS: BENZALKONIUM CHLORIDE 1.3 mg/1 mL
INACTIVE INGREDIENTS: ALOE VERA LEAF; GREEN TEA LEAF; CITRIC ACID MONOHYDRATE; COCAMIDOPROPYL BETAINE; DECYL GLUCOSIDE; GLYCERIN; FD&C GREEN NO. 3; METHYLCHLOROISOTHIAZOLINONE; METHYLISOTHIAZOLINONE; POLYQUATERNIUM-7 (70/30 ACRYLAMIDE/DADMAC; 1600000 MW); POLYSORBATE 20; SODIUM CITRATE; EDETATE SODIUM; WATER; XANTHAN GUM; D&C YELLOW NO. 10

DRUG FACTS

Active ingredient

Benzalkonium Chloride 0.13%

Purpose

Antibacterial

Uses

Helps eliminate bacteria on hands.

Warnings

For exteral use only

When using this product

avoid contact with eyes. If contact occurs, rinse eyes thoroughly with water.

Stop using this product and ask a doctor if

irritation and redness develop and last.

Keep out of reach of children.

In case of accidental ingestion, get medical help or contact a Poison Control Center immediately.

Directions

- use only to refill a Foaming Hand Soap pump bottle.
- apply to dry hands
- work into a rich foamy lather and rinse thoroughly.

Other information

store at room temperature

Inactive ingredients

Aloe Barbadensis Leaf Juice, Camellia Sinensis Leaf Extract, Citric Acid, Cocamidopropyl Betaine, Decyl Glucoside, Fragrance (Parfum), Glycerin, Green 3 (CI 42053), Methylchloroisothiazolinone, Methylisothiazolinone, Polyquaternium-7, Polysorbate 20, Sodium Citrate, Tetrasodium EDTA, Water (Aqua), Xanthan Gum, Yellow 10 (CI 47005).